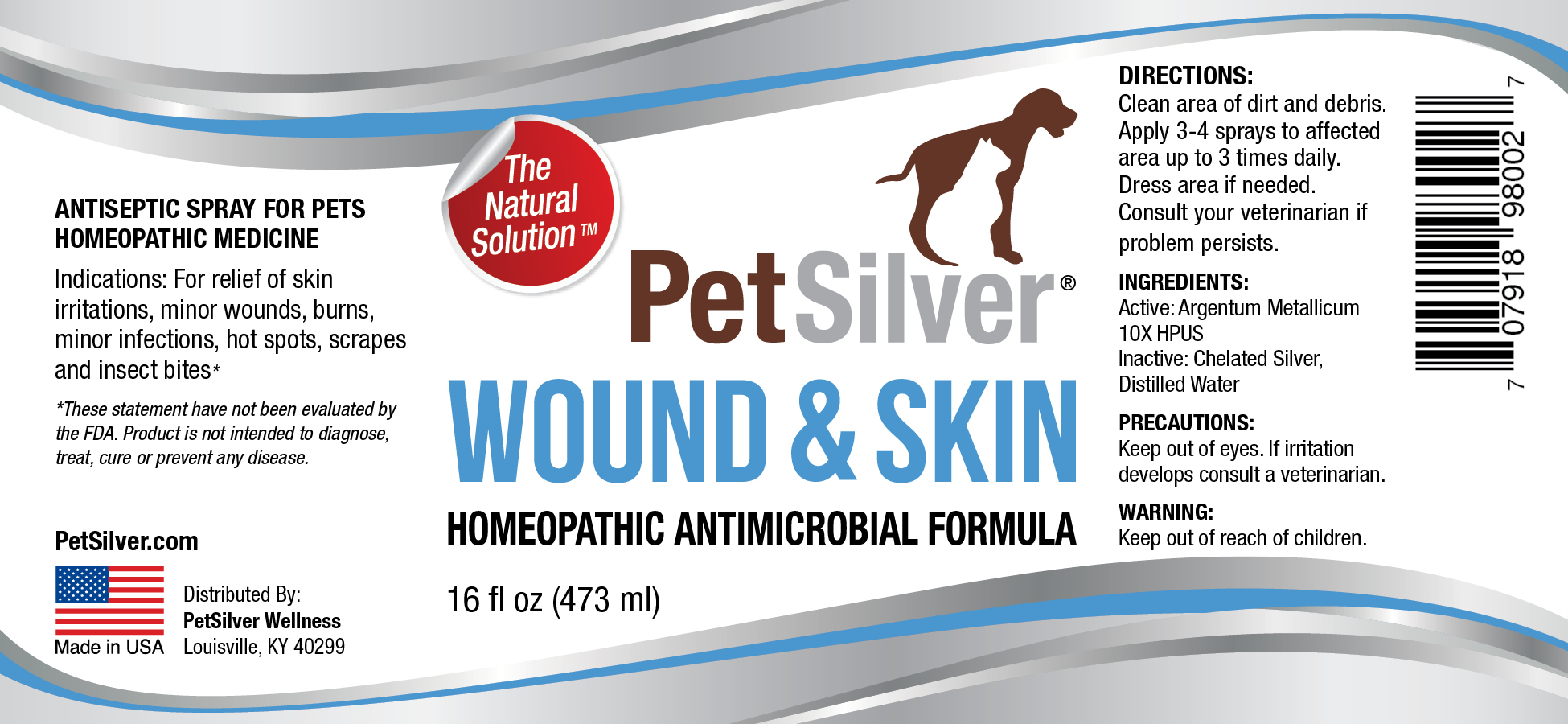 DRUG LABEL: SilvaPlex Wound 16
NDC: 72363-020 | Form: SPRAY
Manufacturer: AG Essence
Category: homeopathic | Type: HUMAN OTC DRUG LABEL
Date: 20251214

ACTIVE INGREDIENTS: SILVER 0.014 g/473 g
INACTIVE INGREDIENTS: WATER 471.914 g/473 g; ANHYDROUS CITRIC ACID 0.072 g/473 g

PetSilver Wound Spray 16

DIRECTIONS:

Clean area of dirt and debris. Apply 3-4 sprays to affected area up to 3 times daily. Dress area if needed. Consult your veterinarian if problem persists.

PRECAUTIONS

Keep out of eyes. If irritation develops consult a veterinarian.

INGREDIENT:

Active: Argentum Metallicum10X HPUS

INGREDIENTS:

Inactive: Chelated Silver, Distilled Water

Indications

For relief of skin irritations, minor wounds, burns, minor infections, hot spots, scrapes and insect bites.

WARNING

Keep out of reach of children

WARNING:

Keep out of reach of children

PetSilver Wound & Skin 16 oz

PetSilver Wound Spray 16 oz